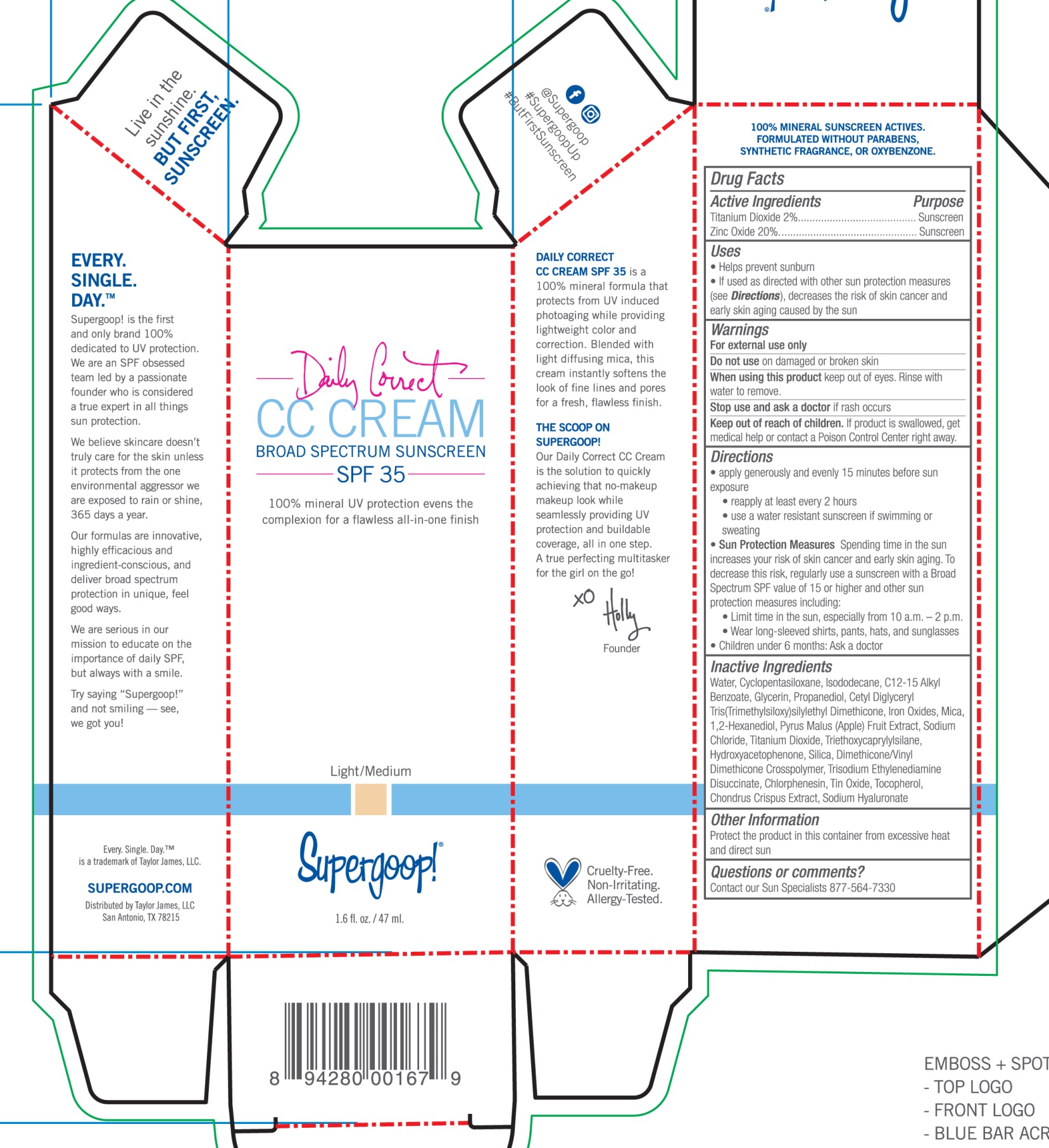 DRUG LABEL: Daily Correct CC Cream Broad Sunscreen SPF 35 Light/Medium
NDC: 75936-203 | Form: CREAM
Manufacturer: Supergoop LLC
Category: otc | Type: HUMAN OTC DRUG LABEL
Date: 20220502

ACTIVE INGREDIENTS: TITANIUM DIOXIDE 2 g/100 mL; ZINC OXIDE 20 g/100 mL
INACTIVE INGREDIENTS: WATER; CYCLOMETHICONE 5; ISODODECANE; ALKYL (C12-15) BENZOATE; GLYCERIN; PROPANEDIOL; FERRIC OXIDE RED; FERRIC OXIDE YELLOW; FERROSOFERRIC OXIDE; MICA; 1,2-HEXANEDIOL; APPLE; SODIUM CHLORIDE; TRIETHOXYCAPRYLYLSILANE; HYDROXYACETOPHENONE; SILICON DIOXIDE; DIMETHICONE/VINYL DIMETHICONE CROSSPOLYMER (SOFT PARTICLE); TRISODIUM ETHYLENEDIAMINE DISUCCINATE; CHLORPHENESIN; STANNIC OXIDE; TOCOPHEROL; CHONDRUS CRISPUS CARRAGEENAN; HYALURONATE SODIUM

Daily Correct CC Cream Broad Sunscreen SPF 35 Light/Medium

Active Ingredients Purpose

Titanium Dioxide 2% Sunscreen

Zinc Oxide 20 % Sunscreen

Uses
· helps prevent sunburn
· If used as directed with other sun protection measures (see Directions), decreases the risk of skin cancer and early skin aging caused by the sun

Keep out of reach of children. If product is swallowed, get medical help or
contact a Poison Control Center right away.

Stop use and ask a doctor if rash occurs

Warnings

For external use only
Do not use on damaged or broken skin
When using this product keep out of eyes. Rinse with water to remove.

Directions
Apply liberally and evenly 15 minutes before sun exposure
Reapply at least every 2 hours
Use a water resistant sunscreen if swimming or sweating
Sun Protection Measures. Spending time in the sun increases your risk of skin
cancer and early skin aging. To decrease this risk, regularly use a sunscreen
with broad spectrum SPF of 15 or higher and other sun protection measures
including:
limit time in the sun, especially from 10 a.m. - 2 p.m.
wear long-sleeve shirts, pants, hats, and sunglasses

Children under 6 months: Ask a doctor

INACTIVE INGREDIENT

Inactive Ingredients Water, Cyclopentasiloxane, C12-15 Alkyl Benzoate, Isododecane, Glycerin, Propanediol, Cetyl Diglyceryl, Tris(Trimethylsiloxy)Silyethyl Dimethicone, Iron Oxides,Mica, 1-2-Hexandiol, Pyrus Malus (Apple) Fruit Extract, Sodium Chloride, Titanium Dioxide, Triethoxycaprylylsilane, Hydroxyacetophenone, Silica, Dimethicone/Vinyl Dimethicone Crosspolymer, Trisodium Ethylenediamine Disuccinate, Chlorphenesin, Tin Oxide, Tocopherol, Chondrus Crispus Extract, Sodium Hyaluronate

PACKAGE LABEL

Daily Correct CC Cream Broad Spectrum Sunscreen SPF 35

Light/Medium

1.6 fl. oz. / 47 ml.